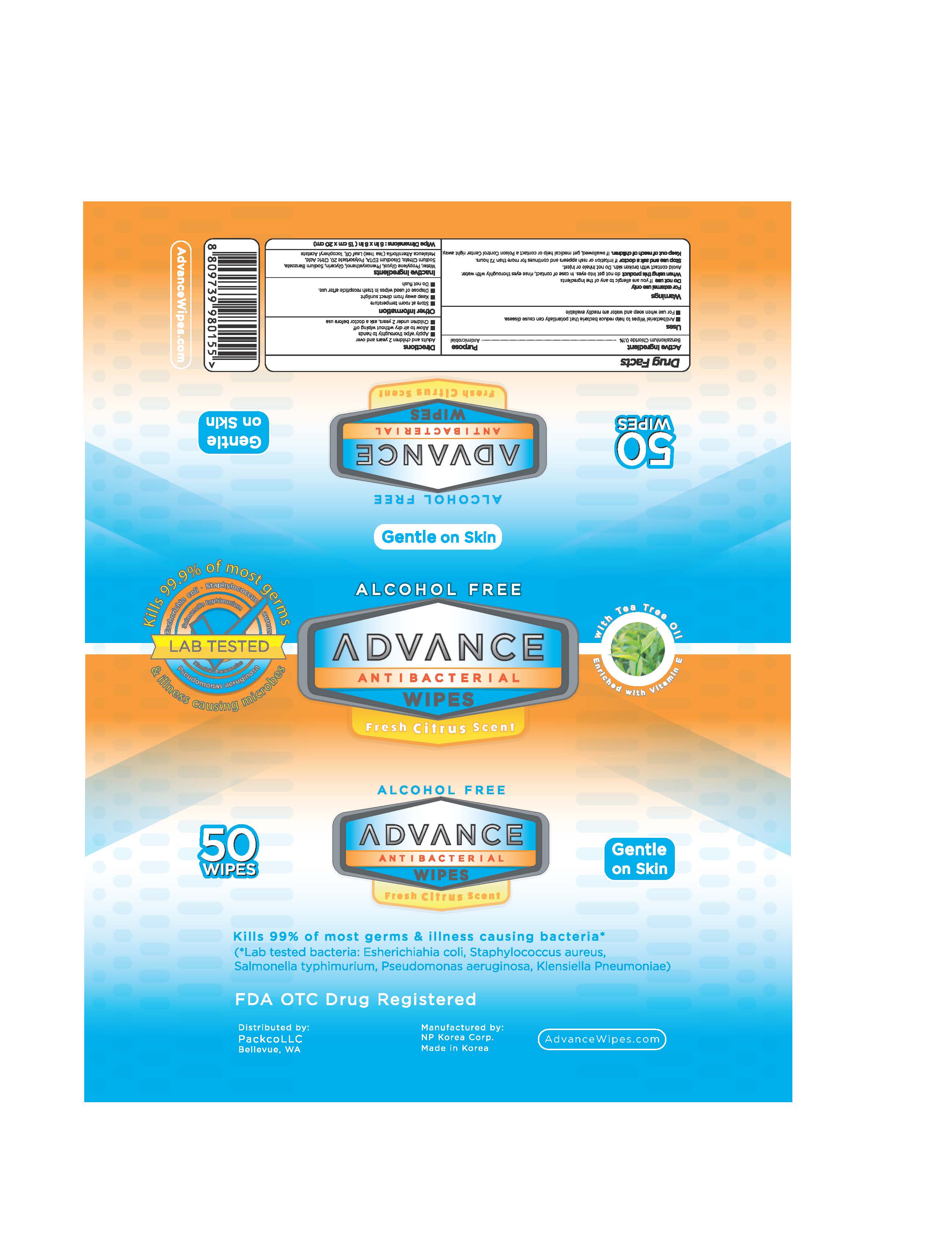 DRUG LABEL: Advance Antibacterial Wipes
NDC: 79178-300 | Form: SWAB
Manufacturer: NP Korea
Category: otc | Type: HUMAN OTC DRUG LABEL
Date: 20210126

ACTIVE INGREDIENTS: BENZALKONIUM CHLORIDE 0.1 1/100 1
INACTIVE INGREDIENTS: GLYCERIN; WATER

Active Ingredient(s)

Benzalkonium Chloride 0.1% ….………………………Antimicrobial

Purpose

Antimicrobial, Hand Wipes

Use

- To help reduce bacteria on the skin.
- For use when soap and water are not available.

Warnings

For external use only.

- Do not use if you are allergic to any of the ingredients.
- Do not get into eyes. In case of contact, rinse eyes thoroughly with water.
- Avoid contact with broken skin.
- Do not inhale or ingest.

Stop use and ask a doctor if irritation or rash occurs. These may be signs of a serious condition.
Keep out of reach of children. If swallowed, get medical help or contact a Poison Control Center right away.

Stop use and ask a doctor if irritation or rash occurs. These may be signs of a serious condition.

Keep out of reach of children. If swallowed, get medical help or contact a Poison Control Center right away.

Directions

Adults and children 2 years and over;

 Apply wipe thoroughly to hands.

 Allow to dry without wiping.

 Children under 2 years, ask a doctor before use.

Other information

- Store at room temperature.
- Keep away from direct sunlight.
- Dispose of used wipes in trash receptacle after use.
- Do not flush.

Inactive ingredients

Water, Propylene Glycol, Phenoxyethanol, Glycerin, Sodium Benzoate, Sodium Citrate, Disodium EDTA, Polysorbate 20, Citric

Acid, Melaleuca Alternifolia (Tea Tree) Leaf Oil, Tocopheryl Acetate.